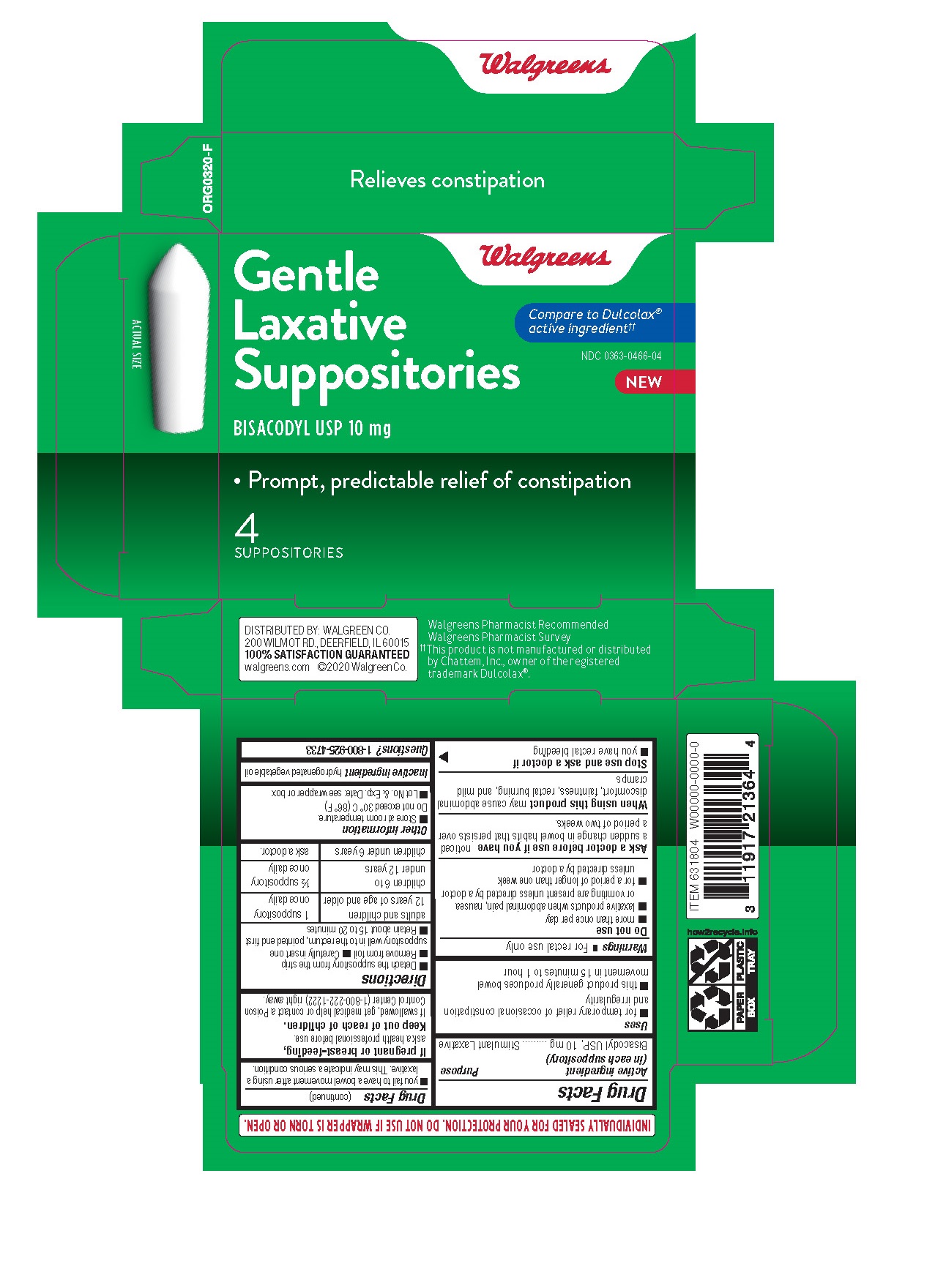 DRUG LABEL: Walgreens Gentle Laxative
NDC: 0363-0466 | Form: SUPPOSITORY
Manufacturer: Walgreens
Category: otc | Type: HUMAN OTC DRUG LABEL
Date: 20260115

ACTIVE INGREDIENTS: BISACODYL 10 mg/1 1
INACTIVE INGREDIENTS: PALM KERNEL OIL

Walgreens®Gentle Laxative 4ct

Active Ingredient (in each Suppository)

Active Ingredient Purpose

(in each Suppository)

Bisacodyl 10 mg.................................Stimulant Laxative

Uses

-for relief of occasional constipation

-this product generally produces bowel movement in 1/4 to 1 hour

Warnings

For rectal use only.

Do not use

-when abdominal pain, nausea, or vomiting are present

-for a period of longer than 1 week

Ask a doctor before use if you have noticed a sudden change in bowel habits that lasts over a period of 2 weeks

When using this product it may cause abdominal discomfort, faintness, rectal burning and mild cramps

Stop use and ask a doctor if

-you have rectal bleeding

-you fail to have a bowel movement after using this product.

This may indicate a serious condition

If pregnant or breast-feeding, ask a health professional before use.

Keep out of reach of children. If swallowed, get medical help or contact a Poison Control Center right away.

Directions

-detach one suppository from the strip

-remove wrapper before inserting into the rectum

adults and children 12 years of age and older 1 suppository once daily

children 6 to under 12 years 1/2 suppository once daily

children under 6 years do not use

Other information

-Store at room temperature. Do not exceed 30oC (86oF)

-Lot No. & Exp. Date: see wrapper or box

Inactive ingredient

Inactive ingredient hydrogenated vegetable oil

Directions

-detach one suppository from the strip
-remove wrapper before inserting into the rectum

adults and children 12 years of age and older 1 suppository once daily
children 6 to under 12 years 1/2 suppository once daily
children under 6 years do not use